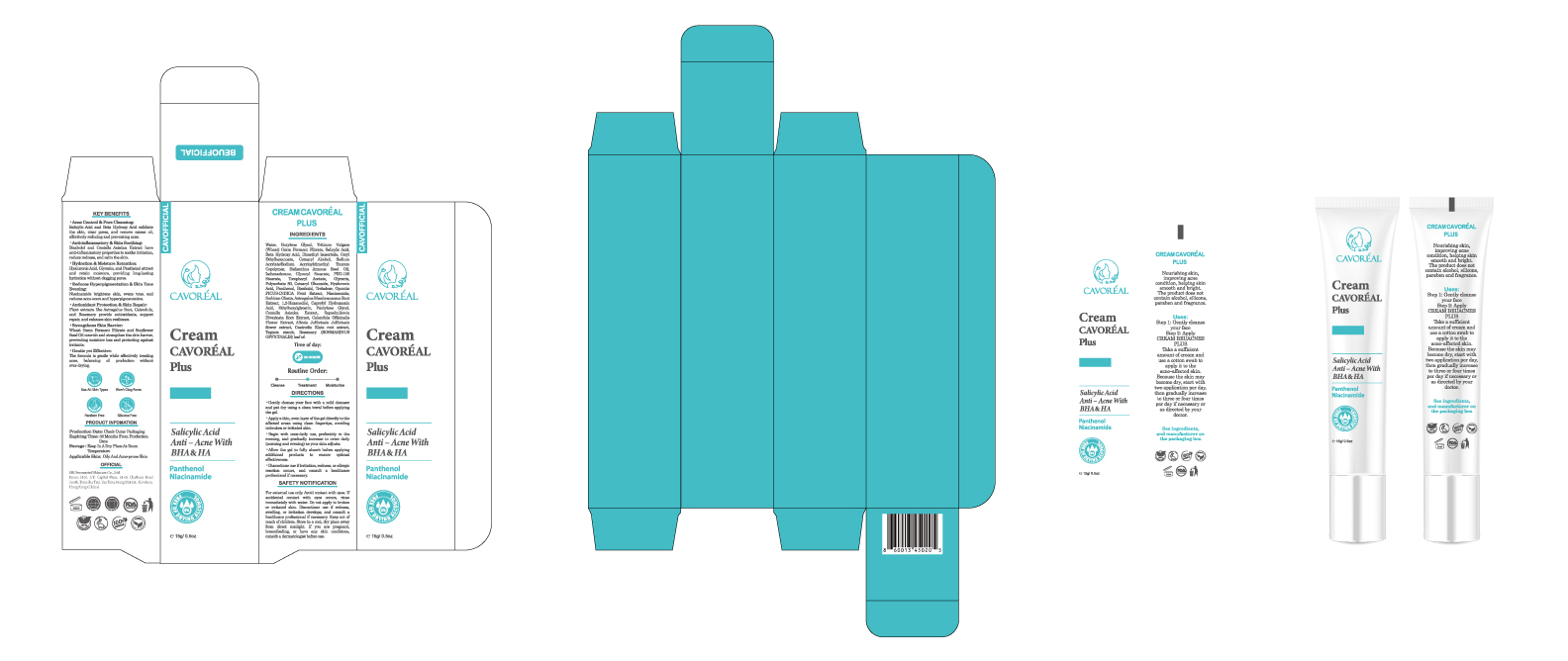 DRUG LABEL: CAVOREAL Plus Salicylic Acid Anti Acne with BHA HA
NDC: 87036-033 | Form: CREAM
Manufacturer: Guangzhou Meijiao Medical Biotechnology Co., Ltd.
Category: otc | Type: HUMAN OTC DRUG LABEL
Date: 20251120

ACTIVE INGREDIENTS: SALICYLIC ACID 1 g/15 g
INACTIVE INGREDIENTS: ALBIZIA JULIBRISSIN FLOWER; CAPRYLHYDROXAMIC ACID; ROSMARINUS OFFICINALIS (ROSEMARY) LEAF OIL; BUTYLENE GLYCOL; HELIANTHUS ANNUUS (SUNFLOWER) SEED OIL; GLYCERYL STEARATE; SAPOSHNIKOVIA DIVARICATA ROOT; TRITICUM VULGARE (WHEAT) GERM; WATER; ALFUZOSIN HYDROXY ACID; BISABOLOL; NIACINAMIDE; ETHYLHEXYLGLYCERIN; CENTELLA ASIATICA; 1,2-HEXANEDIOL; PANTHENOL; HYALURONIC ACID; GASTRODIA ELATA TUBER; PENTYLENE GLYCOL; TREHALOSE; HYDROXYETHYL ACRYLATE/SODIUM ACRYLOYLDIMETHYL TAURATE COPOLYMER (45000 MPA.S AT 1%); POLYSORBATE 80; OPUNTIA FICUS-INDICA; ASTRAGALUS PROPINQUUS ROOT; SORBITAN OLEATE; DIMETHYL ISOSORBIDE; GLYCERIN; CETEARYL ALCOHOL; CALENDULA OFFICINALIS FLOWER; ISOHEXADECANE; CETYL ETHYLHEXANOATE; PEG-100 STEARATE; STARCH, TAPIOCA

Active Ingredient

Salicylic Acid

Inactive Ingredients

Water, Butylene Glycol, Triticum Vulgare (Wheat) Germ Ferment Filtrate, Beta Hydroxy Acid, Dimethyl Isosorbide, Cetyl Ethylhexanoate, Cetearyl Alcohol, Sodium Acrylate/Sodium Acryloyldimethyl Taurate Copolymer, Helianthus Annuus Seed Oil, Isohexadecane, Glyceryl Stearate, PEG-100 Stearate, Tocopheryl Acetate, Glycerin, Polysorbate 80, Cetearyl Glucoside, Hyaluronic Acid, Panthenol, Bisabolol, Trehalose, Opuntia FICUS-INDICA Fruit Extract, Niacinamide, Sorbitan Oleate, Astragalus Membranaceus Root Extract, 1,2-Hexanediol, Caprylyl Hydroxamic Acid, Ethylhexylglycerin, Pentylene Glycol, Centella Asiatica Extract, Saposhnikovia Divaricata Root Extract, Calendula Officinalis Flower Extract, Albizia Julibrissin Julibrissin Flower Extract, Gastrodia Elata Root Extract, Tapioca Starch, Rosemary (ROSMARINUS OFFICINALIS) Leaf Oil

DO NOT USE

SAFETY NOTIFICATION

For external use only. Avoid contact with eyes. If accidental contact with eyes occurs, rinse immediately with water. Do not apply to broken or irritated skin. Discontinue use if redness, swelling, or irritation develops, and consult a healthcare professional if necessary. Keep out of reach of children. Store in a cool, dry place away from direct sunlight. If you are pregnant, breastfeeding, or have any skin conditions, consult a dermatologist before use.

DIRECTIONS

• Gently cleanse your face with a mild cleanser and pat dry using a clean towel before applying the gel.
• Apply a thin, even layer of the gel directly to the affected areas using clean fingertips, avoiding unbroken or irritated skin.
• Begin with once-daily use, preferably in the evening, and gradually increase to twice daily (morning and evening) as your skin adjusts.
• Allow the gel to fully absorb before applying additional products to ensure optimal effectiveness.
• Discontinue use if irritation, redness, or allergic reaction occurs, and consult a healthcare professional if necessary.

WHEN USING

Time of day:

24 HOURS

Routine Order:

Cleanse • Treatment • Moisturize

DIRECTIONS

• Gently cleanse your face with a mild cleanser and pat dry using a clean towel before applying the gel.
• Apply a thin, even layer of the gel directly to the affected areas using clean fingertips, avoiding unbroken or irritated skin.
• Begin with once-daily use, preferably in the evening, and gradually increase to twice daily (morning and evening) as your skin adjusts.
• Allow the gel to fully absorb before applying additional products to ensure optimal effectiveness.
• Discontinue use if irritation, redness, or allergic reaction occurs, and consult a healthcare professional if necessary.

STOP USE

SAFETY NOTIFICATION

For external use only. Avoid contact with eyes. If accidental contact with eyes occurs, rinse immediately with water. Do not apply to broken or irritated skin. Discontinue use if redness, swelling, or irritation develops, and consult a healthcare professional if necessary. Keep out of reach of children. Store in a cool, dry place away from direct sunlight. If you are pregnant, breastfeeding, or have any skin conditions, consult a dermatologist before use.

WARNINGS

SAFETY NOTIFICATION

For external use only. Avoid contact with eyes. If accidental contact with eyes occurs, rinse immediately with water. Do not apply to broken or irritated skin. Discontinue use if redness, swelling, or irritation develops, and consult a healthcare professional if necessary. Keep out of reach of children. Store in a cool, dry place away from direct sunlight. If you are pregnant, breastfeeding, or have any skin conditions, consult a dermatologist before use.

KEEP OUT OF REACH OF CHILDREN

SAFETY NOTIFICATION

For external use only. Avoid contact with eyes. If accidental contact with eyes occurs, rinse immediately with water. Do not apply to broken or irritated skin. Discontinue use if redness, swelling, or irritation develops, and consult a healthcare professional if necessary. Keep out of reach of children. Store in a cool, dry place away from direct sunlight. If you are pregnant, breastfeeding, or have any skin conditions, consult a dermatologist before use.

PURPOSE

KEY BENEFITS

• Acne Control & Pore Cleansing:
Salicylic Acid and Beta Hydroxy Acid exfoliate the skin, clear pores, and remove excess oil, effectively reducing and preventing acne.

• Anti-inflammatory & Skin Soothing:
Bisabolol and Centella Asiatica Extract have anti-inflammatory properties to soothe irritation, reduce redness, and calm the skin.

• Hydration & Moisture Retention:
Hyaluronic Acid, Glycerin, and Panthenol attract and retain moisture, providing long-lasting hydration without clogging pores.

• Reduces Hyperpigmentation & Skin Tone Evening:
Niacinamide brightens skin, evens tone, and reduces acne scars and hyperpigmentation.

• Antioxidant Protection & Skin Repair:
Plant extracts like Astragalus Root, Calendula, and Rosemary provide antioxidants, support repair, and enhance skin resilience.

• Strengthens Skin Barrier:
Wheat Germ Ferment Filtrate and Sunflower Seed Oil nourish and strengthen the skin barrier, preventing moisture loss and protecting against irritants.

• Gentle yet Effective:
The formula is gentle while effectively treating acne, balancing oil production without over-drying.

label

label and box